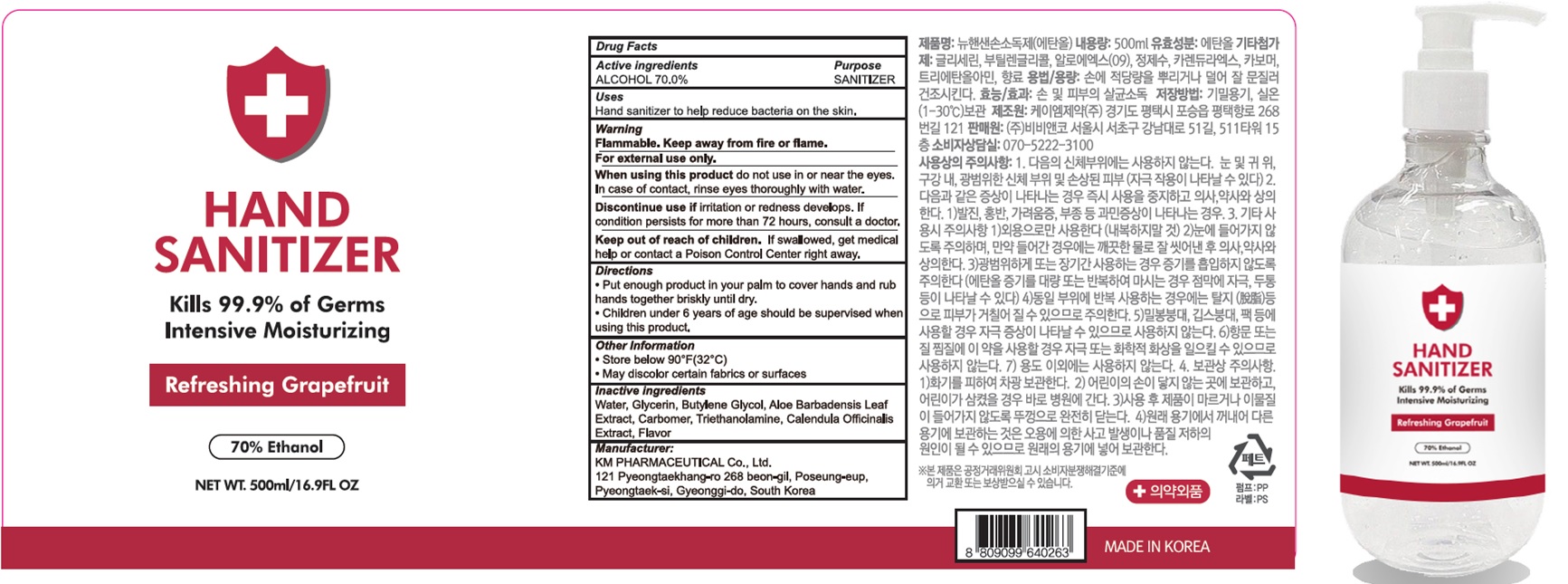 DRUG LABEL: New HANSAN Hand Sanitizer 500mL
NDC: 74080-040 | Form: GEL
Manufacturer: Bb & Co., Ltd.
Category: otc | Type: HUMAN OTC DRUG LABEL
Date: 20200415

ACTIVE INGREDIENTS: ALCOHOL 350.0 g/500 mL
INACTIVE INGREDIENTS: Water; GLYCERIN; Butylene Glycol; ALOE VERA LEAF; CARBOMER HOMOPOLYMER, UNSPECIFIED TYPE; Trolamine; CALENDULA OFFICINALIS FLOWER

Drug Facts

ACTIVE INGREDIENT

ACTIVE INGREDIENT: ALCOHOL 70.0%

INACTIVE INGREDIENT

INACTIVE INGREDIENTS:

Water, Glycerin, Butylene Glycol, Aloe Barbadensis Leaf Extract, Carbomer, Triethanolamine, Calendula Officinalis Extract, Flavor

PURPOSE

PURPOSE: SANITIZER

Keep out of reach of children. If swallowed, get medical help or contact a Poison Control Center right away.

Uses:

Uses : Hand sanitizer to help reduce bacteria on the skin.

WARNINGS

Flammable. Keep away from fire or flame.
For external use only.
When using this product do not use in or near the eyes. In case of contact, rinse eyes thoroughly with water.
Discontinue use if irritation or redness develops. If condition persists for more than 72 hours, consult a doctor.
Keep out of reach of children. If swallowed, get medical help or contact a Poison Control Center right away.

Directions

• Put enough product in your palm to cover hands and rub hands together briskly until dry.
• Children under 6 years of age should be supervised when using this product.

Other Information

• Store below 90°F(32°C)
• May discolor certain fabrics or surfaces